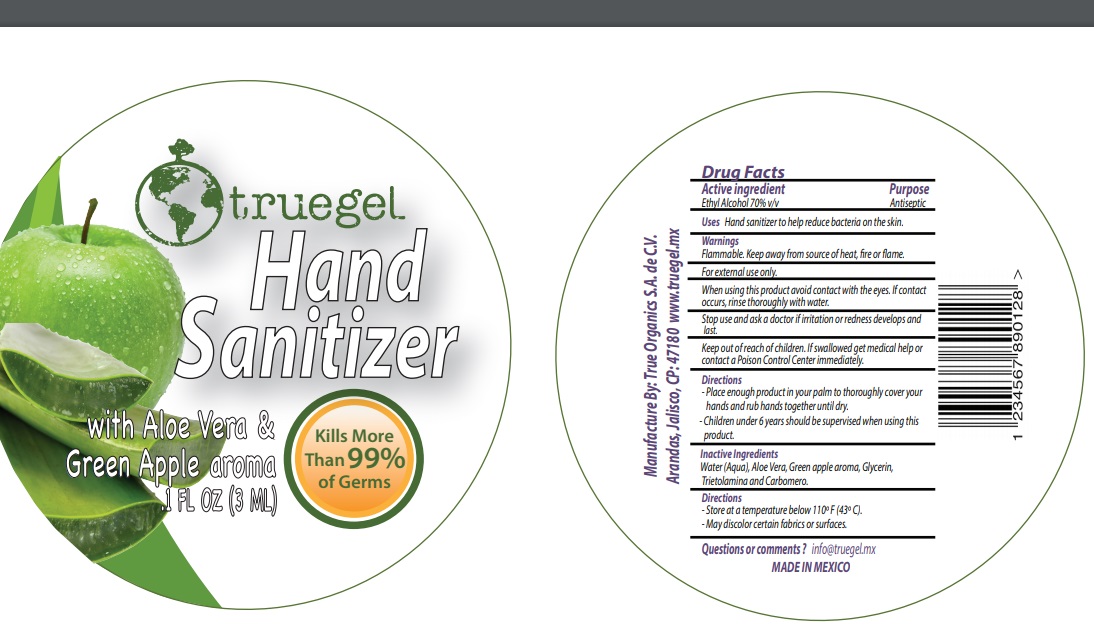 DRUG LABEL: Truegel Hand Sanitizer Aloe Vera and Green Apple Aroma
NDC: 90016-001 | Form: GEL
Manufacturer: True Organics, S.A. de C.V.
Category: otc | Type: HUMAN OTC DRUG LABEL
Date: 20200824

ACTIVE INGREDIENTS: ALCOHOL 0.7 mL/1 mL
INACTIVE INGREDIENTS: WATER; ALOE VERA LEAF; GLYCERIN; TROLAMINE; CARBOMER HOMOPOLYMER, UNSPECIFIED TYPE

Truegel Hand Sanitizer Aloe Vera and Green Apple Aroma

Active ingredient

Ethyl Alcohol 70% v/v

Purpose

Antiseptic

Uses

Hand sanitizer to help reduce bacteria on the skin.

Warnings

Flammable. Keep away from source of heat, fire or flame.

For external use only.

When using this product

avoid contact with the eyes. If contact occurs, rinse thoroughly with water.

Stop use and ask a doctor

if irritation or redness develops and last.

Keep out of reach of children.

If swallowed get medical help or contact a Poison Control Center immediately.

Directions

-Place enough product in your palm to thoroughly cover your hands and rub hands together until dry.

-Children under 6 years should be supervised when using this product.

Inactive Ingredients

Water (Aqua), Aloe Vera, Green apple aroma, Glycerin, Trietolamina and Carbomero.

Directions

-Store at a temperature below 110° F (43° C).

-May discolor certain fabrics or surfaces.

Questions or comments ?

info@truegel.mx